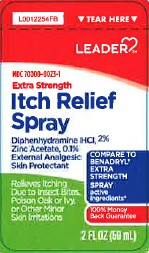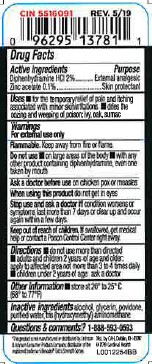 DRUG LABEL: Itch Relief
NDC: 70000-0023 | Form: SPRAY
Manufacturer: Cardinal Health, 110 dba Leader
Category: otc | Type: HUMAN OTC DRUG LABEL
Date: 20260129

ACTIVE INGREDIENTS: DIPHENHYDRAMINE HYDROCHLORIDE 20 mg/1 mL; ZINC ACETATE 1 mg/1 mL
INACTIVE INGREDIENTS: ALCOHOL; GLYCERIN; POVIDONE; WATER; TROMETHAMINE

Leader 295.000/295AB
Itch Relief Spray

Active ingredients

Diphenhydramine HCl 2%
Zinc Acetate 0.1%

Purpose

External analgesic
Skin protectant

Uses

- for the temporary relief of pain and itching associated with minor skin irritations
- dries the oozing and weeping of poison: ivy, oak, sumac

Warnings

For external use only

Flammable

Keep away from fire of flame.

Do not use

- on large areas of the body
- with any other product containing diphenhydramine, even one taken by mouth

Ask a doctor before use

on chicken pox or measles

When using this product

do not get in eyes

Stop use and ask a doctor if

condition worsens or symptoms last more than 7 days or clear up and occur again within a few days

Keep out of reach of children.

If swallowed, get medical help or contact a Poison Control Center right away.

Directions

- do not use more than directed
- adults and children 2 years of age and older: apply to affected area not more than 3 to 4 times daily
- children under 2 years of age: ask a doctor

Other information

• store at 20⁰ - 25⁰C (68⁰ - 77⁰F)

Inactive ingredients

alcohol, glycerin, povidone, purified water, tris (hydroxymethyl)aminomethane

Questions & comments?

1-888-593-0593

Disclaimer

*This product is not manufactured or distributed by Johnson & Johnson Consumer Products Company of the registered trademark BenadrylExtra Strength Spray.

Adverse reactions

Dist. by CAH, Dublin, OH 43017

2019 Cardinal Health

principal display panel

TEAR HERE

LEADER™

NDC 70000-0023-1

Extra Strength

Itch Relief Spray

Diphenhydramine HCI, 2%

Zinc Acetate, 0.1%

External Analgesic

Skin Protectant

COMPARE TO BENADRYL®EXTRA STRENGTH SPRAY active ingredients*

100% Money Back Guarantee

Relieves Itching

Due to Insect Bites,

Poison Oak or Ivy, or Other Minor Skin Irritations

2 FL OZ (59 mL)